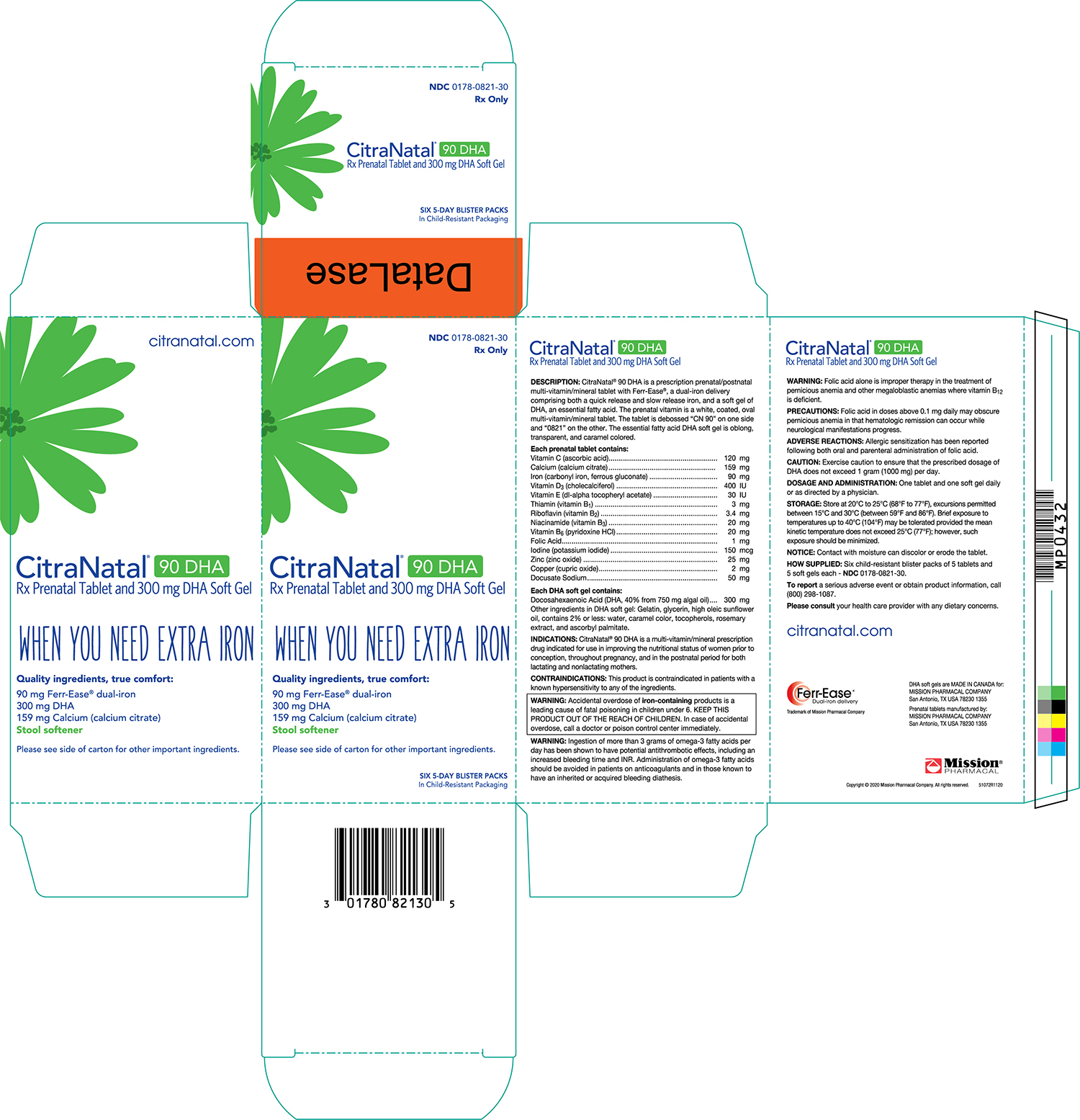 DRUG LABEL: CitraNatal 90 DHA
NDC: 0178-0821 | Form: TABLET
Manufacturer: Mission Pharmacal Company
Category: prescription | Type: HUMAN PRESCRIPTION DRUG LABEL
Date: 20240108

ACTIVE INGREDIENTS: ASCORBIC ACID 120 mg/1 1; IRON 85 mg/1 1; .ALPHA.-TOCOPHEROL ACETATE 30 [iU]/1 1; THIAMINE 3 mg/1 1; NIACINAMIDE 20 mg/1 1; PYRIDOXINE HYDROCHLORIDE 20 mg/1 1; FOLIC ACID 1 mg/1 1; ZINC OXIDE 25 mg/1 1; CUPRIC OXIDE 2 mg/1 1; DOCUSATE SODIUM 50 mg/1 1; CALCIUM CITRATE 159 mg/1 1; THIAMINE MONONITRATE 4.54 mg/1 1; POTASSIUM IODIDE 150 ug/1 1; FERROUS GLUCONATE 5 mg/1 1; VITAMIN D 400 [iU]/1 1; RIBOFLAVIN 3.4 mg/1 1

CitraNatal®90 DHA

BOXED WARNING

WARNING:Accidental overdose of iron-containingproducts is a leading cause of fatal poisoning in children under 6. KEEP THIS PRODUCT OUT OF THE REACH OF CHILDREN. In case of accidental overdose, call a doctor or poison control center immediately.

DESCRIPTION

CitraNatal®90 DHA is a prescription prenatal/postnatal multivitamin/mineral tablet with Ferr-Ease®, a patented dual-iron delivery comprising both a quick release and slow release iron, and a capsule of an essential fatty acid. The prenatal vitamin is a white, oval multivitamin/mineral tablet. The tablet is debossed “CN 90” on one side and “0821” on the other. The essential fatty acid DHA capsule is caramel colored and contains a light yellow to orange semi-solid mixture.

Each prenatal tablet contains:
Vitamin C (Ascorbic acid) | 120 mg
Calcium (Calcium citrate) | 159 mg
Iron (Carbonyl iron, ferrous gluconate) | 90 mg
Vitamin D3 (Cholecalciferol) | 400 IU
Vitamin E (dl-alpha tocopheryl acetate) | 30 IU
Thiamin (Vitamin B1) | 3 mg
Riboflavin (Vitamin B2) | 3.4 mg
Niacinamide (Vitamin B3) | 20 mg
Vitamin B6 (Pyridoxine HCl) | 20 mg
Folic Acid | 1 mg
Iodine (Potassium iodide) | 150 mcg
Zinc (Zinc oxide) | 25 mg
Copper (Cupric oxide) | 2 mg
Docusate Sodium | 50 mg

Each DHA gelatin capsule contains:
Docosahexaenoic
Acid(DHA, 40% from 750 mg Algal Oil) | 300 mg
Eicosapentaenoic Acid (EPA) | Not more than 0.750 mg

Other ingredients in DHA gelatin capsule: Gelatin, glycerin, sunflower oil, water, caramel color, tocopherols, rosemary extract, sunflower lecithin, ascorbyl palmitate.

INDICATIONS

CitraNatal®90 DHA is a multivitamin/mineral prescription drug indicated for use in improving the nutritional status of women prior to conception, throughout pregnancy, and in the postnatal period for both lactating and nonlactating mothers.

CONTRAINDICATIONS

This product is contraindicated in patients with a known hypersensitivity to any of the ingredients.

WARNING

Ingestion of more than 3 grams of omega-3 fatty acids per day has been shown to have potential antithrombotic effects, including an increased bleeding time and INR. Administration of omega-3 fatty acids should be avoided in patients on anticoagulants and in those known to have an inherited or acquired bleeding diathesis.

WARNING:Folic acid alone is improper therapy in the treatment of pernicious anemia and other megaloblastic anemias where vitamin B12is deficient.

PRECAUTIONS

Folic acid in doses above 0.1 mg daily may obscure pernicious anemia in that hematologic remission can occur while neurological manifestations progress.

ADVERSE REACTIONS

Allergic sensitization has been reported following both oral and parenteral administration of folic acid.

DOSAGE AND ADMINISTRATION

One tablet and one capsule daily or as directed by a physician.

STORAGE

Store at 20-25°C (68-77°F)

NOTICE:Contact with moisture can discolor or erode the tablet.

HOW SUPPLIED

Six child-resistant blister packs of 5 tablets and 5 capsules each - NDC0178-0821-30

To reporta serious adverse event or obtain product information, call (210) 696-8400.

Please consultyour health care provider with any dietary concerns.

51072R1120

DHA capsules manufactured for:
MISSION PHARMACAL COMPANY
San Antonio, TX USA 78230 1355
Prenatal tablets manufactured by:
MISSION PHARMACAL COMPANY
San Antonio, TX USA 78230 1355

Ferr-Ease™
Dual-iron delivery

Trademark of Mission Pharmacal Company

PACKAGE LABEL

CitraNatal® 90DHA Carton
NDC: 0178-0821-30